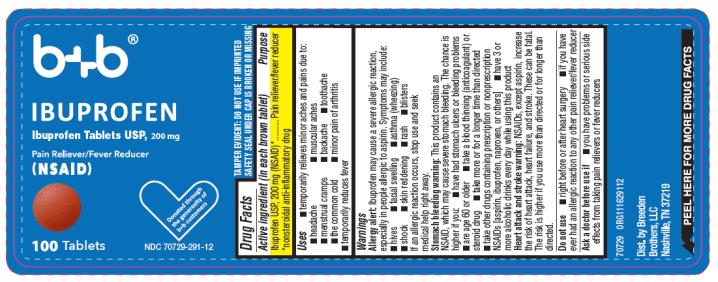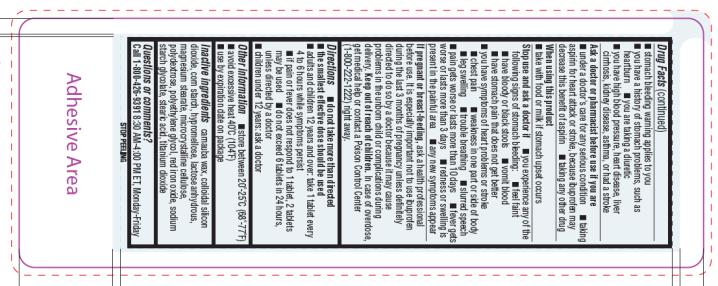 DRUG LABEL: Ibuprofen
NDC: 70729-291 | Form: TABLET, FILM COATED
Manufacturer: Breeden Brothers, LLC
Category: otc | Type: HUMAN OTC DRUG LABEL
Date: 20180406

ACTIVE INGREDIENTS: IBUPROFEN 200 mg/1 1
INACTIVE INGREDIENTS: CARNAUBA WAX; SILICON DIOXIDE; STARCH, CORN; HYPROMELLOSE, UNSPECIFIED; ANHYDROUS LACTOSE; MAGNESIUM STEARATE; MICROCRYSTALLINE CELLULOSE; POLYDEXTROSE; POLYETHYLENE GLYCOL, UNSPECIFIED; FERRIC OXIDE RED; SODIUM STARCH GLYCOLATE TYPE A POTATO; STEARIC ACID; TITANIUM DIOXIDE

Brown Ibuprofen Tablets

Drug Facts

22 words

Active ingredient (in each brown tablet)

Ibuprofen USP,

200 mg (NSAID)*

*nonsteroidal anti-inflammatory drug

Purpose

Pain reliever/fever reducer

Uses

26 words

- temporarily relieves minor aches and pains due to:
  • headache
  • toothache
  • backache
  • menstrual cramps
  • the common cold
  • muscular aches
  • minor pain of arthritis
- temporarily reduces fever

Warnings

53 words

See carton for complete warnings (short label only)
See vial card for complete warnings (vial label only)
Allergy alert: Ibuprofen may cause a severe allergic reaction, especially in people allergic to aspirin.
Symptoms may include:
• hives
• facial swelling
• asthma (wheezing)
• shock
• skin reddening
• rash
• blisters
If an allergic reaction occurs, stop use and seek medical help right away.

Stomach bleeding warning: This product contains an NSAID, which may cause severe stomach 74 words
bleeding. The chance is higher if you:
• are age 60 or older
• have had stomach ulcers or bleeding problems
• take a blood thinning (anticoagulant) or steroid drug
• take other drugs containing prescription or nonprescription NSAIDs [aspirin, ibuprofen,
naproxen, or others]
• have 3 or more alcoholic drinks every day while using this product
• take more or for a longer time than directed

Heart attack and stroke warning: NSAIDs, except aspirin, increase the risk of heart attack, heart failure, 37 words
and stroke. These can be fatal. The risk is higher if you use more than directed or for longer than directed.

Do not use

24 words

• if you have ever had an allergic reaction to any other pain reliever/fever reducer

• right before or after heart surgery

Ask a doctor before use if

57 words

• stomach bleeding warning applies to you
• you have problems or serious side effects from taking pain relievers or fever reducers
• you have a history of stomach problems, such as heartburn
• you have high blood pressure, heart disease, liver cirrhosis, kidney disease, asthma, or
had a stroke
• you are taking a diuretic

Ask a doctor or pharmacist before use if you are

37 words

• under a doctor's care for any serious condition
• taking aspirin for heart attack or stroke, because ibuprofen may decrease this benefit of aspirin
• taking any other drug

When using this product

13 words
• take with food or milk if stomach upset occurs

Stop use and ask a doctor if

89 words

- you experience any of the following signs of stomach bleeding:
  • feel faint
  • vomit blood • have bloody or black stools
  • have stomach pain that does not get better
- you have symptoms of heart problems or stroke
  • chest pain
  • trouble breathing
  • weakness in one part or side of body
  • slurred speech
  • leg swelling
- pain gets worse or lasts more than 10 days
- fever gets worse or lasts more than 3 days
- redness or swelling is present in the painful area
- any new symptoms appear

If pregnant or breast-feeding,

ask a health professional before use. It is especially important not 70 words
to use ibuprofen during the last 3 months of pregnancy unless definitely directed to do so by a doctor because it may cause problems in the unborn child or complications during delivery.

Keep out of reach of children.

In case of overdose, get medical help or contact a Poison Control Center (1-800-222-1222) right away.

Directions

67 words

- do not take more than directed
- the smallest effective dose should be used
- adults and children 12 years and over: take 1 tablet every 4 to 6 hours while symptoms persist
  • if pain or fever does not respond to 1 tablet, 2 tablets may be used
  • do not exceed 6 tablets in 24 hours, unless directed by a doctor
- children under 12 years: ask a doctor

Other information

- 63 words
  TAMPER EVIDENT: DO NOT USE IF IMPRINTED SAFETY SEAL UNDER CAP IS BROKEN OR MISSING (short label only)
- TAMPER EVIDENT: DO NOT USE IF OUTER PACKAGE IS OPENED OR BLISTER IS TORN OR BROKEN (blister package only)
- store between 20˚-25˚C (68˚-77˚F)
- avoid excessive heat 40˚C (104˚F)
- see end flap for expiration date and lot number (carton only)
- use by expiration date on package (vial card, vial label & label only)

Inactive ingredients

carnauba wax, colloidal silicon dioxide, corn starch, hypromellose, lactose 29 words
anhydrous, magnesium stearate, microcrystalline cellulose, polydextrose, polyethylene glycol, red iron oxide, sodium starch glycolate, stearic acid, titanium dioxide

Questions or comments?

12 words
Call 1-800-426-9391 8:30 AM-4:00 PM ET, Monday-Friday
(or specific to customer’s labeling guide)

Additional Information:
• Change to version 44-291.09 BBW1116
• In Legend Box update DF version to 44-291.09

PRINCIPAL DISPLAY PANEL

NDC 70729-291-12
b + b
IBUPROFEN
Ibuprofen Tablets USP, 200 mg
Pain Reliever/ Fever Reducer
(NSAID)
100 Tablets